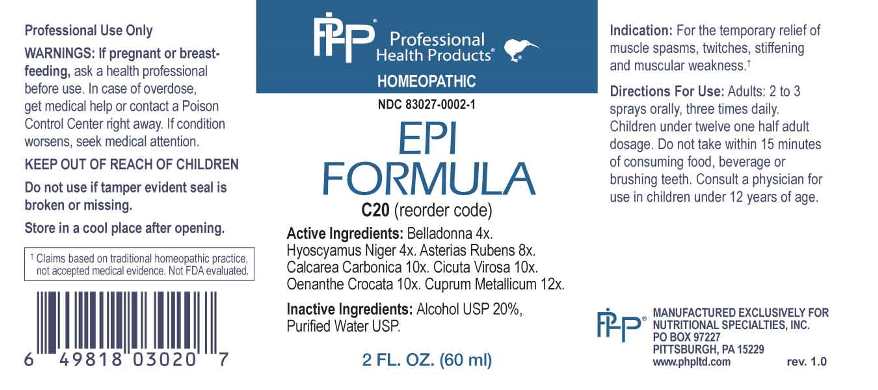 DRUG LABEL: EPI Formula
NDC: 83027-0002 | Form: SPRAY
Manufacturer: Nutritional Specialties, Inc.
Category: homeopathic | Type: HUMAN OTC DRUG LABEL
Date: 20240605

ACTIVE INGREDIENTS: ATROPA BELLADONNA 4 [hp_X]/1 mL; HYOSCYAMUS NIGER 4 [hp_X]/1 mL; ASTERIAS RUBENS 8 [hp_X]/1 mL; OYSTER SHELL CALCIUM CARBONATE, CRUDE 10 [hp_X]/1 mL; CICUTA VIROSA ROOT 10 [hp_X]/1 mL; OENANTHE CROCATA ROOT 10 [hp_X]/1 mL; COPPER 12 [hp_X]/1 mL
INACTIVE INGREDIENTS: WATER; ALCOHOL

DRUG FACTS:

ACTIVE INGREDIENTS:

Belladonna 4X, Hyoscyamus Niger 4X, Asterias Rubens 8X, Calcarea Carbonica 10X, Cicuta Virosa 10X, Oenanthe Crocata 10X, Cuprum Metallicum 12X.

PURPOSE:

For the temporary relief of muscle spasms, twitches, stiffening and muscular weakness.†

†Claims based on traditional homeopathic practice, not accepted medical evidence. Not FDA evaluated.

WARNINGS:

Professional Use Only

If pregnant or breast-feeding, ask a health professional before use.

In case of overdose, get medical help or contact a Poison Control Center right away.

If condition worsens, seek medical attention.

KEEP OUT OF REACH OF CHILDREN

Do not use if tamper evident seal is broken or missing.

Store in a cool place after opening

KEEP OUT OF REACH OF CHILDREN:

In case of overdose, get medical help or contact a Poison Control Center right away.

DIRECTIONS:

Adults: 2 to 3 sprays orally, three times daily. Children under twelve one half adult dosage. Do not take within 15 minutes of consuming food, beverage or brushing teeth. Consult a physician for use in children under 12 years of age.

INDICATIONS:

For the temporary relief of muscle spasms, twitches, stiffening and muscular weakness.†

†Claims based on traditional homeopathic practice, not accepted medical evidence. Not FDA evaluated.

INACTIVE INGREDIENTS:

Alcohol USP 20%, Purified Water USP.

QUESTIONS:

MANUFACTURED EXCLUSIVELY FOR

NUTRITIONAL SPECIALTIES, INC.

PO BOX 97227

PITTSBURG, PA 15229

www.phpltd.com

PACKAGE LABEL DISPLAY:

Professional

Health Products

HOMEOPATHIC

NDC 83027-0002-1

EPI

FORMULA

2 FL. OZ (60 ml)